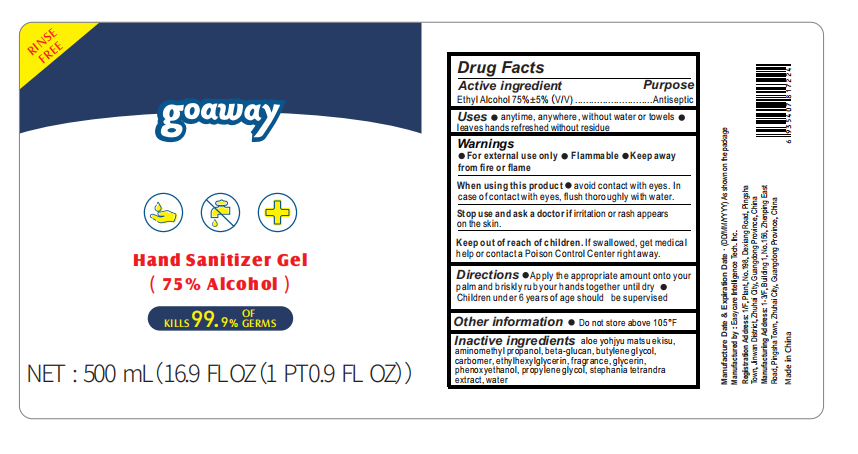 DRUG LABEL: Hand Sanitizer Gel(75% Alcohol)
NDC: 56045-006 | Form: GEL
Manufacturer: Easycare Intelligence Tech. Inc.
Category: otc | Type: HUMAN OTC DRUG LABEL
Date: 20200421

ACTIVE INGREDIENTS: ALCOHOL 375 mL/500 mL
INACTIVE INGREDIENTS: CURDLAN; GLYCERIN; PROPYLENE GLYCOL; WATER; AMINOMETHYLPROPANOL; ETHYLHEXYLGLYCERIN; POLYACRYLIC ACID (250000 MW); BUTYLENE GLYCOL; ALOE; STEPHANIA TETRANDRA WHOLE; PHENOXYETHANOL

When using this product●avoid contact with eyes. In case of contact with eyes, flush thoroughly with water.
Stop use and ask a doctor if irritation or rash appears on the skin.

INACTIVE INGREDIENT

Inactive ingre dients aloe yohjyu matsuekisu,aminomethyl pr opanol, beta-glucan, butyiene glyool,carbomer, ethyhexylglycerin, fragr ance, ghycerin,.phenoxyethanol, propyleneglycol, stephania tetrandra extrad. water

PURPOSE

Disinfection
Sterilization
No Rinseing

keep out of reach of children

ACTIVE INGREDIENT

alcohol

INDICATIONS AND USAGE

●Apply the appropriate amount onto your palm and briskly rub your hands together until dry

●Children under 6 years of age should be supervised

DOSAGE AND ADMINISTRATION

●For external use only ●Flammable:Keep away from fire or flame